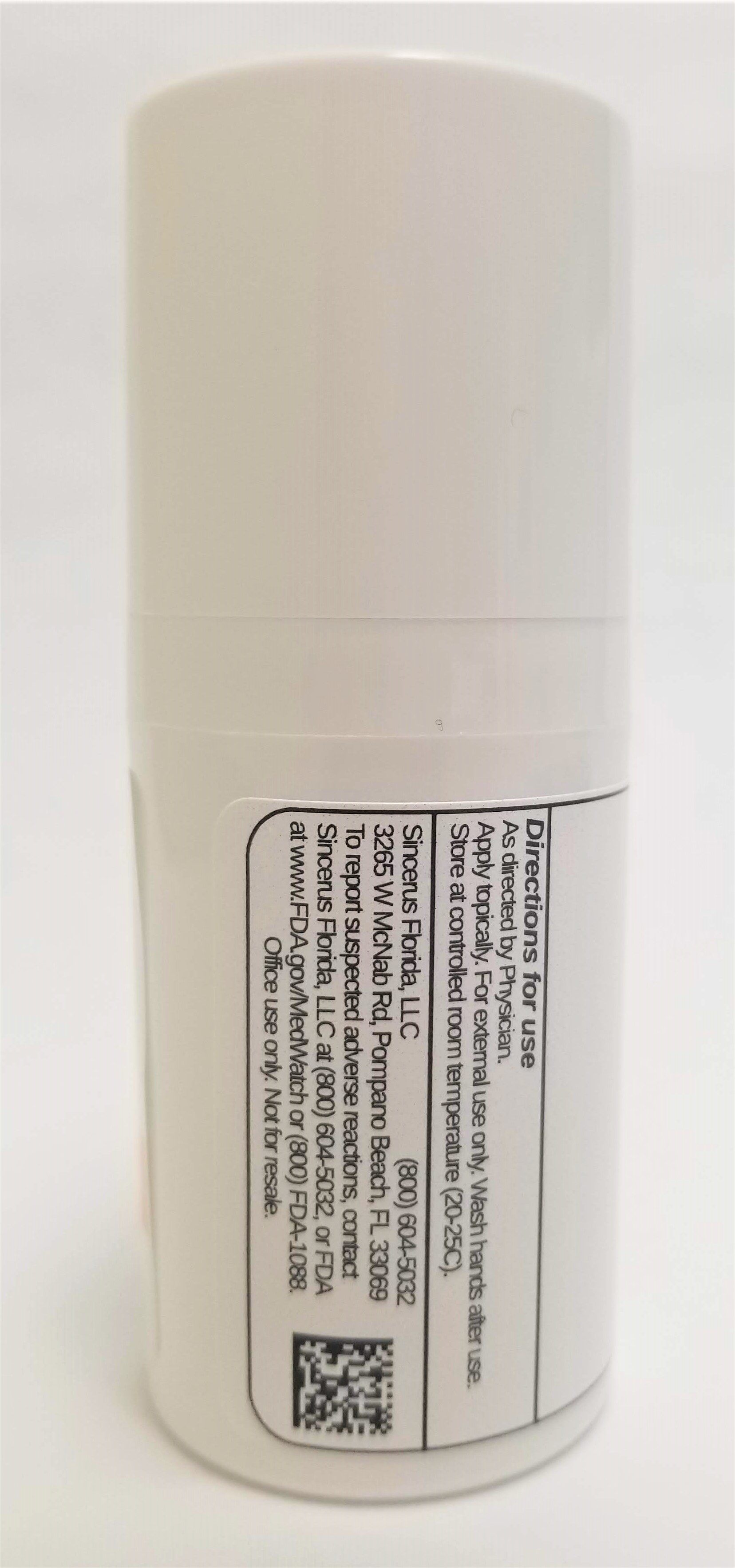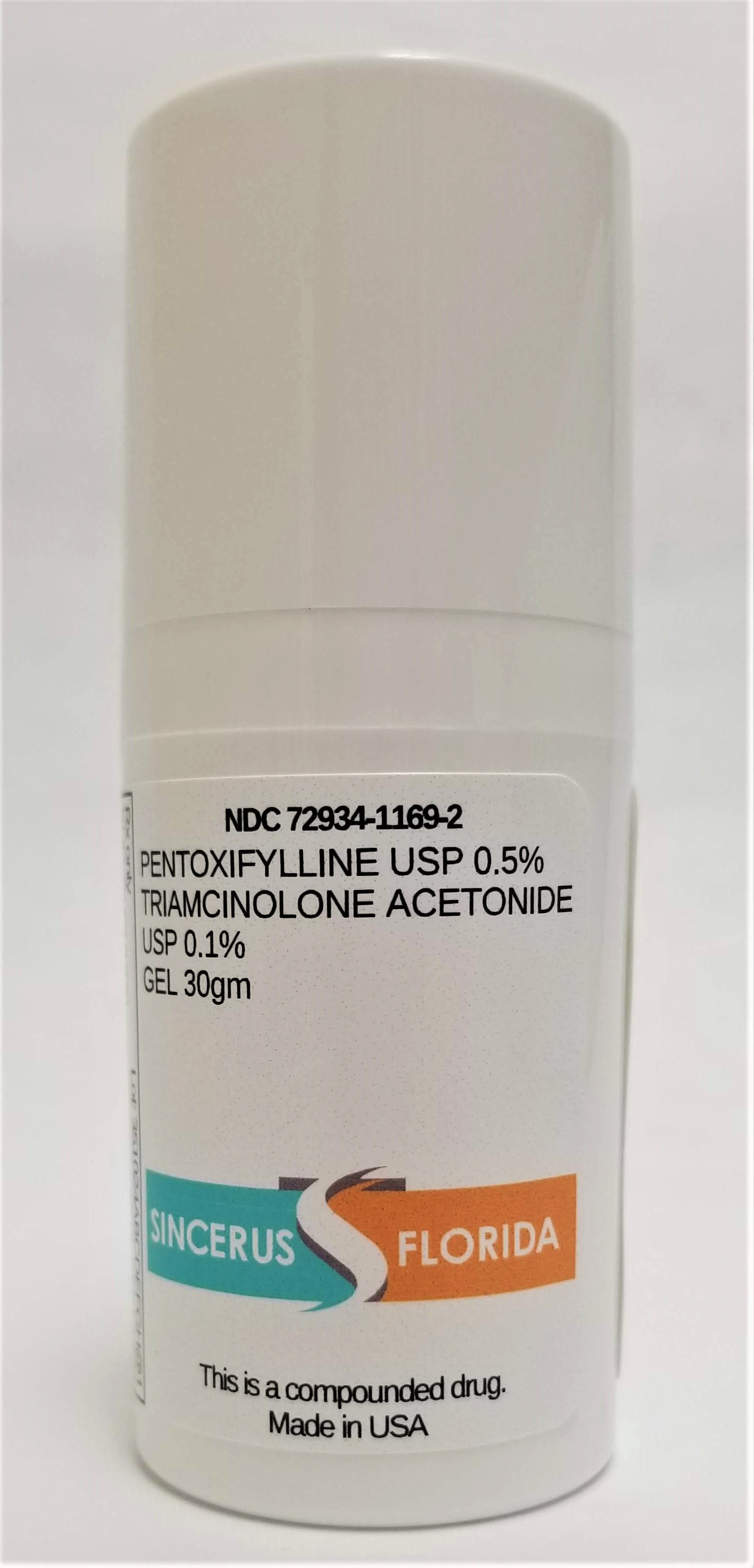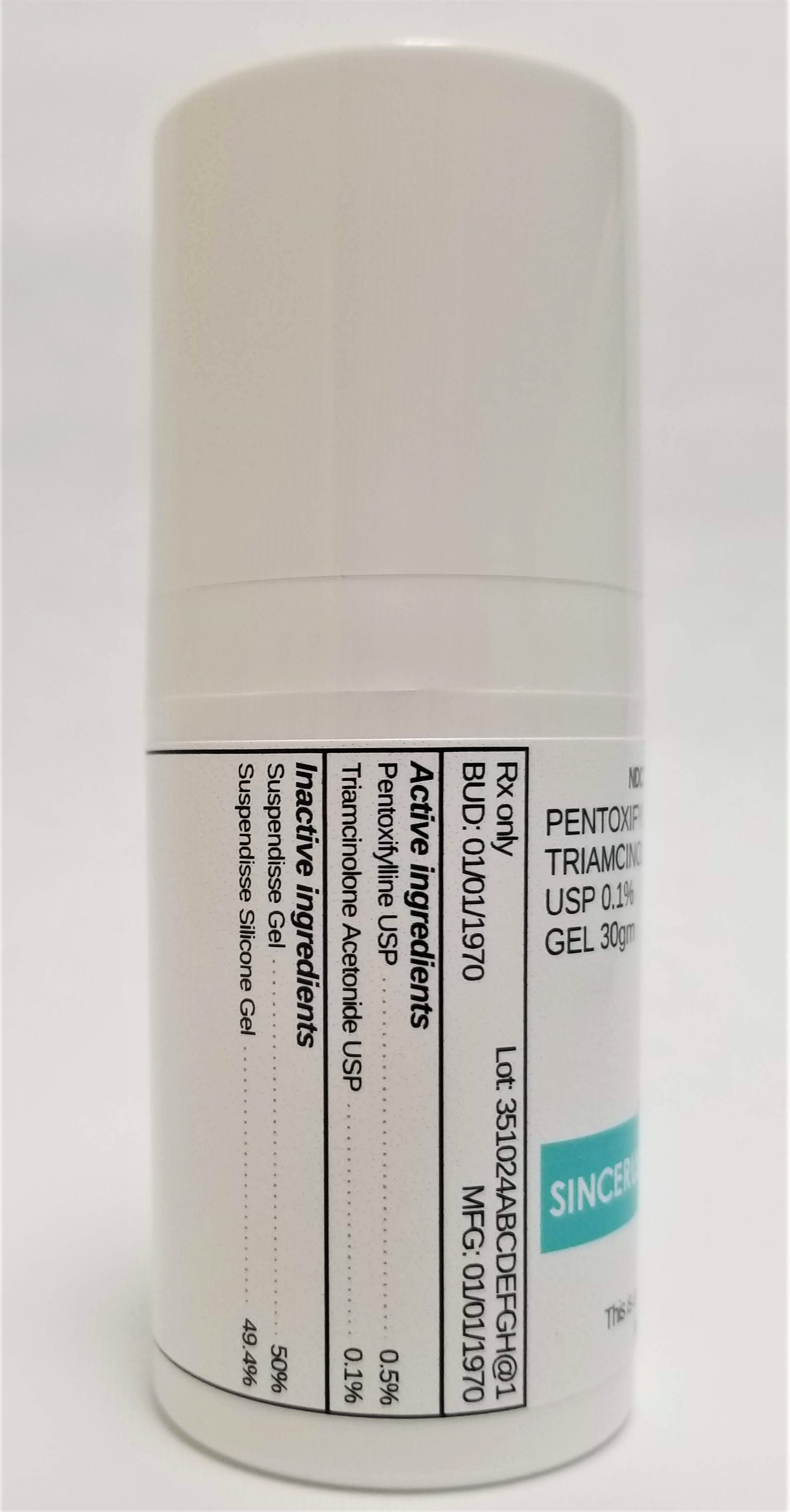 DRUG LABEL: PENTOXIFYLLINE 0.5% / TRIAMCINOLONE ACETONIDE 0.1%
NDC: 72934-1169 | Form: GEL
Manufacturer: Sincerus Florida, LLC
Category: prescription | Type: HUMAN PRESCRIPTION DRUG LABEL
Date: 20190514

ACTIVE INGREDIENTS: PENTOXIFYLLINE 0.5 g/100 g; TRIAMCINOLONE ACETONIDE 0.1 g/100 g

PENTOXIFYLLINE 0.5% / TRIAMCINOLONE ACETONIDE 0.1%